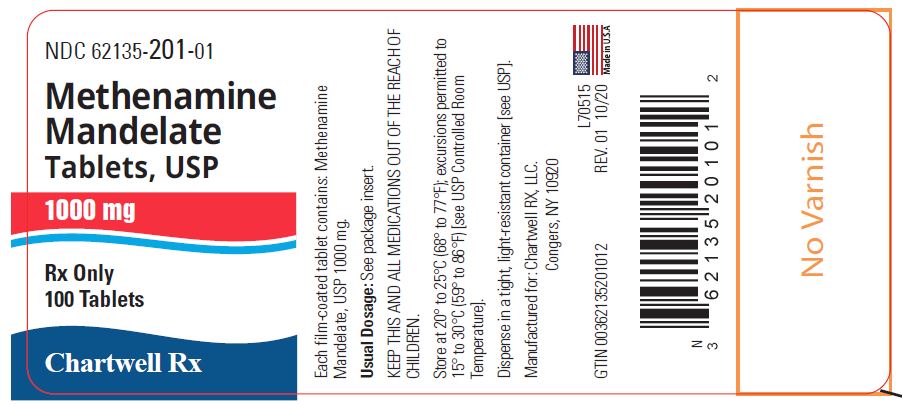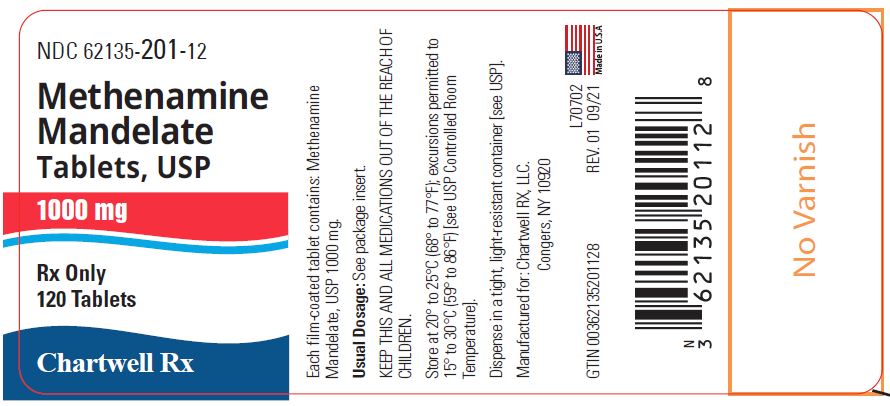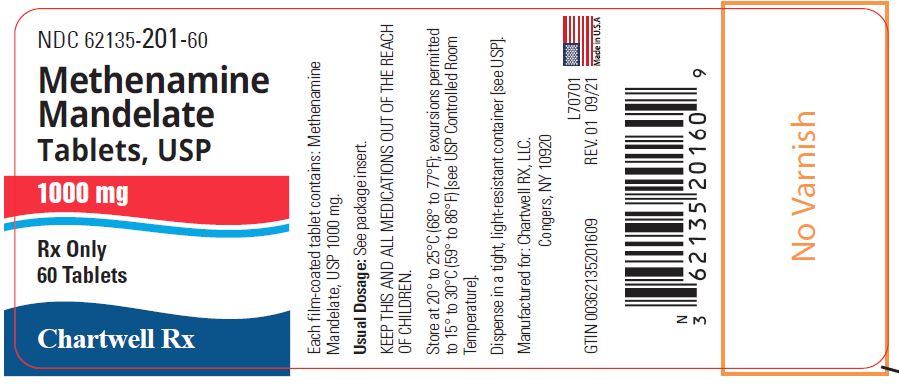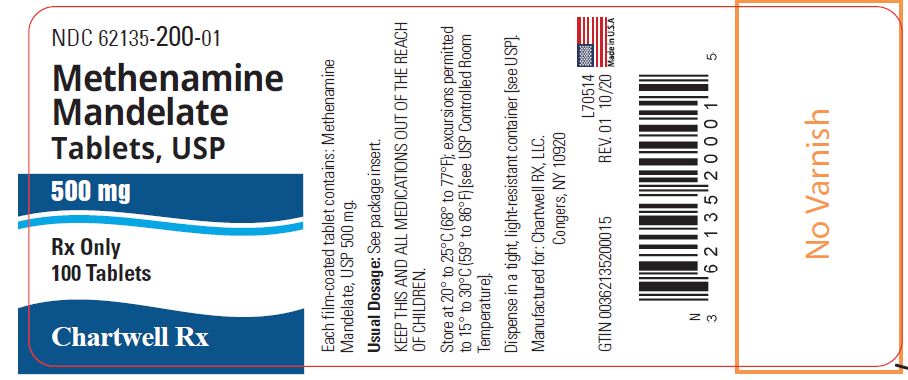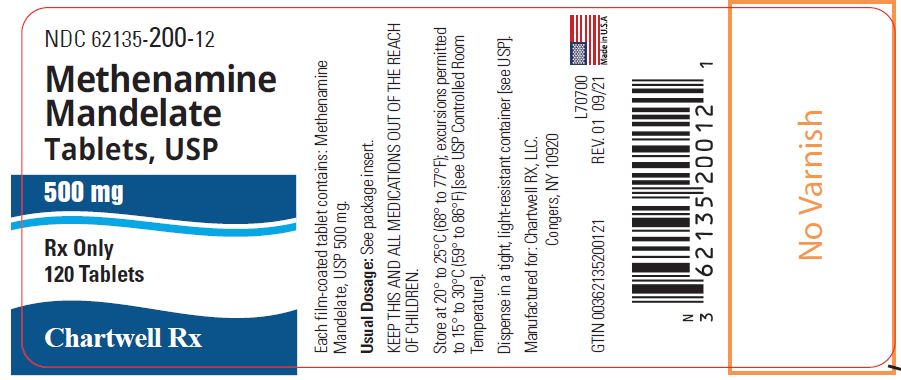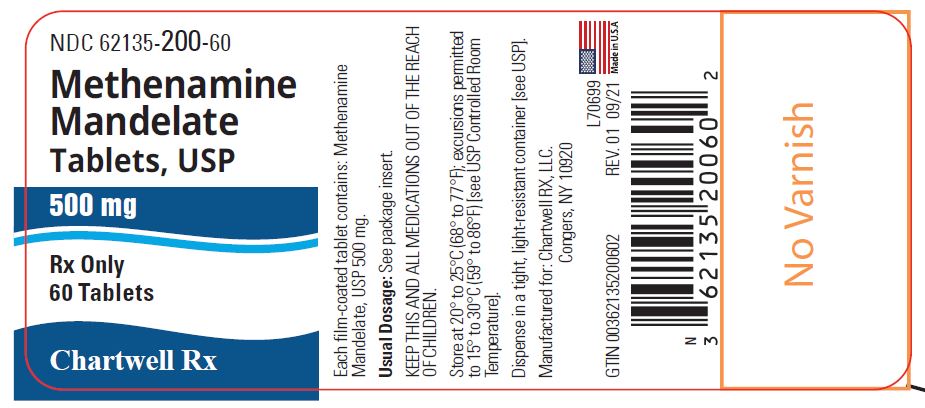 DRUG LABEL: Methenamine Mandelate
NDC: 62135-200 | Form: TABLET, FILM COATED
Manufacturer: Chartwell RX, LLC
Category: prescription | Type: HUMAN PRESCRIPTION DRUG LABEL
Date: 20230710

ACTIVE INGREDIENTS: METHENAMINE MANDELATE 500 mg/1 1
INACTIVE INGREDIENTS: CROSCARMELLOSE SODIUM; FD&C BLUE NO. 2--ALUMINUM LAKE; MAGNESIUM STEARATE; MICROCRYSTALLINE CELLULOSE; POLYETHYLENE GLYCOL, UNSPECIFIED; POLYVINYL ALCOHOL, UNSPECIFIED; SILICON DIOXIDE; TALC; TITANIUM DIOXIDE

Methenamine Mandelate Tablets, USP
Rx Only

DESCRIPTION

Methenamine mandelate, a urinary antibacterial agent, is the chemical combination of mandelic acid with methenamine. Methenamine mandelate is available for oral use as film-coated tablets.

Methenamine mandelate tablets contain 500 mg and 1000 mg (1 g) methenamine mandelate and the following inactive ingredients: croscarmellose sodium, FD&C blue #2 aluminum lake, magnesium stearate, microcrystalline cellulose, polyethylene glycol, polyvinyl alcohol, silicon dioxide, talc and titanium dioxide.

CLINICAL PHARMACOLOGY

Methenamine mandelate is readily absorbed but remains essentially inactive until it is excreted by the kidneys and concentrated in the urine. An acid urine is essential for antibacterial action, with maximum efficacy occurring at pH 5.5 or less. In an acid urine, mandelic acid exerts its antibacterial action and also contributes to the acidification of the urine. Mandelic acid is excreted both by glomerular filtration and tubular excretion. The methenamine component is hydrolyzed in acid urine to ammonia and to the bactericidal agent formaldehyde.

Proportionally less formaldehyde is released as urinary pH approaches 6.0 and insufficient quantities are released above this level for therapeutic response. There is equally effective antibacterial activity against both gram-positive and gram-negative organisms, since the antibacterial action of mandelic acid and formaldehyde is nonspecific. There are reports that methenamine mandelate is ineffective in some infections with Proteus vulgaris and urea-splitting strains of Pseudomonas aeruginosa and A. aerogenes. Since urea-splitting strains may raise the pH of the urine, particular attention to supplementary acidification with agents such as ascorbic acid, and urinary pH monitoring is required. However, results in any single case will depend to a large extent on the underlying pathology and the overall management.

INDICATIONS AND USAGE

Methenamine mandelate is indicated for the suppression or elimination of bacteriuria associated with pyelonephritis, cystitis, and other chronic urinary tract infections; also those neurologic diseases leading to an infected residual urine. When used as recommended, methenamine mandelate is particularly suitable for long-term therapy because of its safety and because resistance to the nonspecific bactericidal action of formaldehyde does not develop. Pathogens resistant to other antibacterial agents may respond to methenamine mandelate because of the nonspecific effect of formaldehyde formed in an acid urine.

Prophylactic Use Rationale: Urine is a good culture medium for many urinary pathogens. Inoculation by a few organisms (relapse or reinfection) may lead to bacteriuria in susceptible individuals. Thus, the rationale of management in recurring urinary tract infection (bacteriuria) is to change the urine from a growth-supporting to a growth-inhibiting medium. There is a growing body of evidence that long-term administration of methenamine mandelate can prevent the recurrence of bacteriuria in patients with chronic pyelonephritis.

Therapeutic Use Rationale: Methenamine mandelate helps to sterilize the urine, and in some situations in which underlying pathologic conditions prevent sterilization by any means, it can help to suppress the bacteriuria. Methenamine mandelate should not be used alone for acute infections with parenchymal involvement causing systemic symptoms such as chills and fever. A thorough diagnostic investigation as a part of the overall management of the urinary tract infection should accompany the use of methenamine mandelate.

CONTRAINDICATIONS

Methenamine mandelate tablets are contraindicated in patients with renal insufficiency, severe hepatic disease, severe dehydration, and in patients who have exhibited hypersensitivity to any components of this product.

WARNINGS

Methenamine mandelate should be avoided in patients with gout because it may precipitate urate crystals in their urine. A similar situation may arise in patients with a predisposition to the formation of uric acid stones.

Methenamine preparations should not be given to patients taking sulfonamides because some sulfonamides may form an insoluble precipitate with formaldehyde in the urine.

PRECAUTIONS

General

Dysuria may occur (usually at higher than recommended dosage). This can be controlled by reducing the dosage and the acidification. When urine acidification is contraindicated or unattainable (as with some urea-splitting bacteria), the drug is not recommended.

Large doses of methenamine (8 g daily for 3 to 4 weeks) have caused bladder irritation, painful and frequent micturition, albuminuria, and gross hematuria.

Information for Patients

To assure an acidic pH, patients should be instructed to restrict or avoid milk products and antacids containing sodium carbonate or bicarbonate.

Laboratory Tests

As with all urinary tract infections, the efficacy of therapy should be monitored by repeated urine cultures. Urinary pH monitoring is required to assure an acidic

urinary pH (below 5.5).

Drug Interactions

Formaldehyde and sulfamethizole form an insoluble precipitate in acid urine; therefore, methenamine mandelate should not be administered concurrently with sulfamethizole or other sulfonamides. Concurrent use of salicylates may lead to increased serum salicylate levels since excretion of salicylates is reduced in acidified urine.

Drug/Laboratory Test Interactions

Formaldehyde interferes with fluorometric procedures for determination of urinary catecholamines and vanillylmandelic acid (VMA), causing erroneously high results. Formaldehyde also causes falsely decreased urine estriol levels by reacting with estriol when acid hydrolysis techniques are used; estriol determinations which use enzymatic hydrolysis are unaffected by formaldehyde.

Formaldehyde causes falsely elevated 17-hydroxycorticosteroid levels when the Porter-Silber method is used and falsely decreased 5-hydroxyindoleacetic acid (5HIAA) levels by inhibiting color development when nitrosonaphthol methods are used.

CARCINOGENESIS and MUTAGENESIS

Methenamine mandelate has not been evaluated for carcinogenicity or mutagenicity.

Methenamine was evaluated for mutagenicity in the Ames Salmonella/mammalian microsome test. Five strains of Salmonella typhimurium (TA98, TA100, TA1535, TA1537 and TA1538) and a strain of Escherichia coli (WP2uvrA) were used. At a dose of 10,000 μg/plate methenamine showed mutagenic activity in Salmonella typhimurium TA98 and TA100 by metabolic activation and also showed mutagenic activity in TA98 without microsomal activation.

In one large study, no evidence of carcinogenicity was found following long-term oral administration of methenamine 1.25 g/kg/day to rats (104 weeks) and mice (60 weeks).

Pregnancy

Teratogenic Effects. Pregnancy Category C.

Animal reproduction studies have not been conducted with methenamine mandelate. It is also not known whether methenamine mandelate can cause fetal harm when administered to a pregnant woman or can affect reproduction capacity. Since methenamine is known to cross the placental barrier, methenamine mandelate should be given to a pregnant woman only if the potential benefit outweighs the risk.

Nursing Mothers

Methenamine is excreted in breast milk. Because of the potential for serious adverse reactions in nursing infants, a decision should be made whether to discontinue nursing or to discontinue the drug, taking into account the importance of the drug to the mother.

ADVERSE REACTIONS

Gastrointestinal disturbances (nausea, stomach upset), generalized skin rash, dysuria, painful or difficult urination may occur occasionally with the use of methenamine preparations. Microscopic and rarely, gross hematuria have been described.

OVERDOSAGE

Minimize absorption by inducing vomiting or by gastric lavage followed by administration of activated charcoal. Administer orally fluids and alkalinize with sodium bicarbonate.

DOSAGE AND ADMINISTRATION

The average adult dose is 4 g a day given as one 1000 mg tablet or two 500 mg tablets after each meal and at bedtime. Children 6 to 12 years of age should receive half the adult dose; one 500 mg tablet, 4 times a day.

HOW SUPPLIED

Methenamine Mandelate Tablets, USP 500 mg are blue, unscored, oval, film-coated, debossed with "CE 34" on one side and plain on the other side.

Supplied in bottles of 60 (NDC 62135-200-60)
Supplied in bottles of 100 (NDC 62135-200-01)
Supplied in bottles of 120 (NDC 62135-200-12)

Methenamine Mandelate Tablets, USP 1000 mg (1 g) are blue, unscored, oval, film-coated, debossed with "CE 35" on one side and plain on the other side.

Supplied in bottles of 60 (NDC 62135-201-60)
Supplied in bottles of 100 (NDC 62135-201-01)
Supplied in bottles of 120 (NDC 62135-201-12)

Preserve in well-closed containers

Store at 20° to 25°C (68° to 77°F); excursions permitted to 15° to 30°C (59° to 86°F) [see USP Controlled Room Temperature].

Manufactured for:
Chartwell RX LLC.
Congers, NY 10920
Made in USA
L70516 Rev. 09/2021

PACKAGE LABEL-PRINCIPAL DISPLAY PANEL

Methenamine Mandelate Tablets, USP 500 mg - NDC 62135-200-60 - 60 Tablets Label

Methenamine Mandelate Tablets, USP 500 mg - NDC 62135-200-01 - 100 Tablets Label

Methenamine Mandelate Tablets, USP 500 mg - NDC 62135-200-12 - 120 Tablets Label

Methenamine Mandelate Tablets, USP 1000 mg - NDC 62135-201-60 - 60 Tablets Label

Methenamine Mandelate Tablets, USP 1000 mg - NDC 62135-201-01 - 100 Tablets Label

Methenamine Mandelate Tablets, USP 1000 mg - NDC 62135-201-12 - 120 Tablets Label